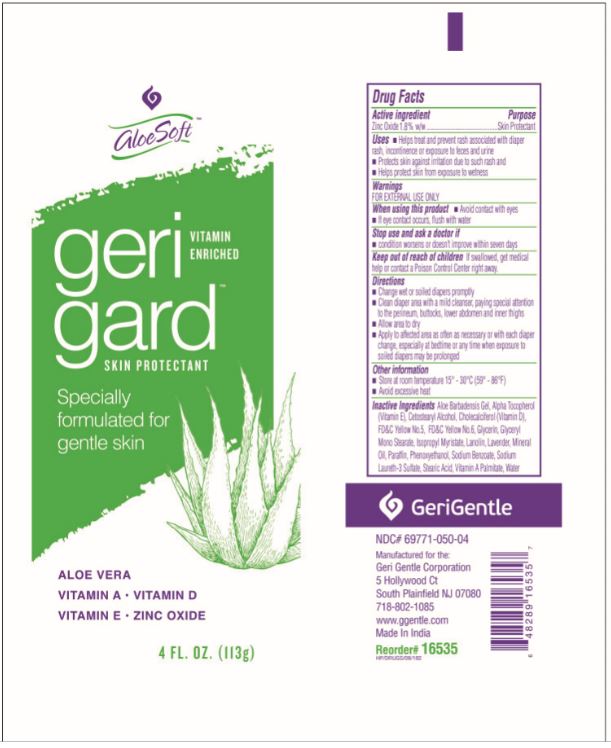 DRUG LABEL: GeriGard
NDC: 69771-050 | Form: OINTMENT
Manufacturer: Geri-Gentle Corporation
Category: otc | Type: HUMAN OTC DRUG LABEL
Date: 20251027

ACTIVE INGREDIENTS: ZINC OXIDE 18 mg/1 g
INACTIVE INGREDIENTS: ALOE VERA LEAF; ALPHA-TOCOPHEROL; CETETH-10; CETOSTEARYL ALCOHOL; CETYL ALCOHOL; CHOLECALCIFEROL; GLYCERIN; LANOLIN; METHYLPARABEN; MINERAL OIL; PARAFFIN; PETROLATUM; PHENOXYETHANOL; POLYETHYLENE GLYCOL 6000; POLYSORBATE 60; PROPYLPARABEN SODIUM; STEARETH-20; TROLAMINE; VITAMIN A; WATER

GeriGard

Active ingredient

Zinc Oxide (1.8% w/w)

Purpose

Skin Prorectant

Uses:

- Helps treat and prevent diaper rash.
- Helps seal out wetness.
- Dries the oozing and weeping of:
- poison ivy
- poison oak
- poison sumac

Warnings:

For external use only

When using this product

- Do not get into eyes

Stop use nd ask a doctor if:

- Condition worsens
- Symptoms last more than 7 days or clear up and occur again in a few days, consult a physician

Keep out of reach of children

- If swallowed, get medical help or contact a Poison Control Center right away

Directions:

- Apply liberally as needed
- For diaper rash:
- change wet and soiled diapers promptly
- allow to dry
- Apply ointment liberally with each diaper change

Other information:

- Store at room temperature 15º - 30ºC (59º - 86ºF)
- Avoid excessive heat
- Contains color additives including FD&C Yellow No. 5 (Tartrazine).

Inactive ingredients:

Aloe Vera Leaf, Alpha-Tocopherol, Ceteth-10, Cetostearyl Alcohol, Cetyl Alcohol, Cholecalciferol, Glycerin, Lanolin, Lavender, Methylparaben, Mineral Oil, Paraffin, Petrolatum, Phenoxyethanol, Polyethylene Glycol 6000, Polysorbate 60, Propylparaben Sodium, Steareth-20, Trolamine, Vitamin A, Water.